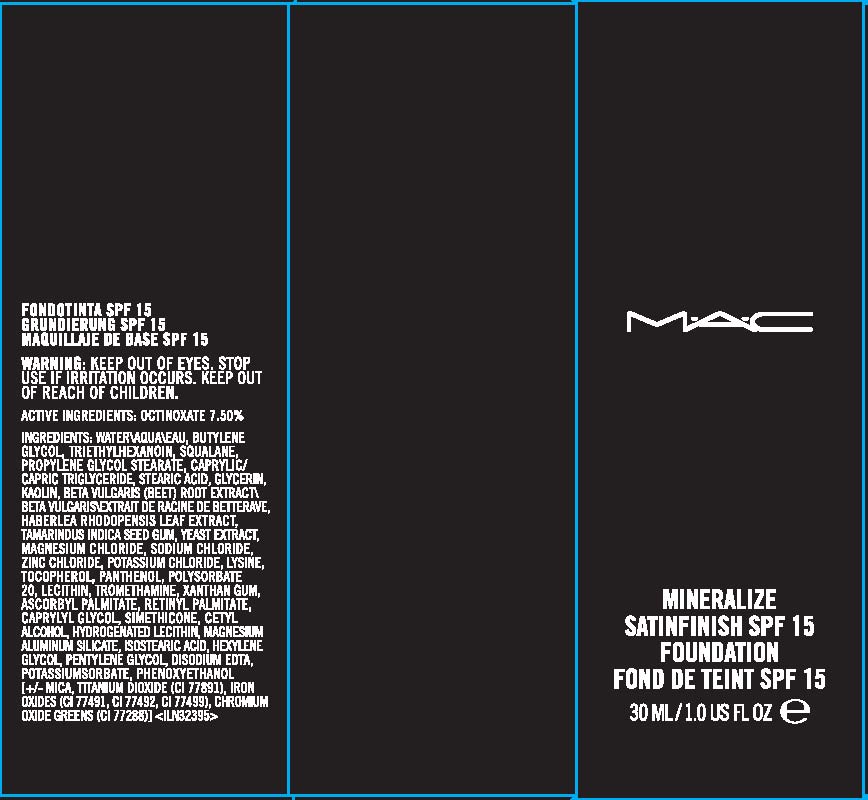 DRUG LABEL: MINERALIZE
NDC: 40046-0042 | Form: LIQUID
Manufacturer: MAKEUP ART COSMETICS
Category: otc | Type: HUMAN OTC DRUG LABEL
Date: 20110518

ACTIVE INGREDIENTS: OCTINOXATE 7.5 mL/100 mL
INACTIVE INGREDIENTS: WATER; BUTYLENE GLYCOL; SQUALANE; ISOSTEARIC ACID; GLYCERIN; KAOLIN; STEARIC ACID; MEDIUM-CHAIN TRIGLYCERIDES; BEET; YEAST; MAGNESIUM CHLORIDE; SODIUM CHLORIDE; ZINC CHLORIDE; POTASSIUM CHLORIDE; LYSINE; ALPHA-TOCOPHEROL, DL-; PANTHENOL; POLYSORBATE 20; LECITHIN, SOYBEAN; TROMETHAMINE; XANTHAN GUM; ASCORBYL PALMITATE; VITAMIN A PALMITATE; 2-OCTANOL; CETYL ALCOHOL; HYDROGENATED SOYBEAN LECITHIN; MAGNESIUM ALUMINUM SILICATE; HEXYLENE GLYCOL; PENTYLENE GLYCOL; EDETATE DISODIUM ANHYDROUS  ; POTASSIUM SORBATE; PHENOXYETHANOL; MICA; TITANIUM DIOXIDE; FERRIC OXIDE RED; FERRIC OXIDE YELLOW; FERROSOFERRIC OXIDE

ACTIVE INGREDIENT: OCTINOXATE 7.5%

INACTIVE INGREDIENT

INACTIVE INGREDIENTS: WATER [] BUTYLENE GLYCOL [] TRIETHYLHEXANOIN [] SQUALANE [] PROPYLENE GLYCOL STEARATE [] CAPRYLIC/CAPRIC TRIGLYCERIDE [] STEARIC ACID [] GLYCERIN [] KAOLIN [] BETA VULGARIS (BEET) ROOT EXTRACT [] HABERLEA RHODOPENSIS LEAF EXTRACT [] TAMARINDUS INDICA SEED GUM [] YEAST EXTRACT [] MAGNESIUM CHLORIDE [] SODIUM CHLORIDE [] ZINC CHLORIDE [] POTASSIUM CHLORIDE [] LYSINE [] TOCOPHEROL [] PANTHENOL [] POLYSORBATE 20 [] LECITHIN [] TROMETHAMINE [] XANTHAN GUM [] ASCORBYL PALMITATE [] RETINYL PALMITATE [] CAPRYLYL GLYCOL [] SIMETHICONE [] CETYL ALCOHOL [] HYDROGENATED LECITHIN [] MAGNESIUM ALUMINUM SILICATE [] ISOSTEARIC ACID [] HEXYLENE GLYCOL [] PENTYLENE GLYCOL [] DISODIUM EDTA [] POTASSIUM SORBATE [] PHENOXYETHANOL [] [+/- MICA [] TITANIUM DIOXIDE (CI 77891) [] IRON OXIDES (CI 77491, CI 77492, CI 77499) [] CHROMIUM OXIDE GREENS (CI 77288)]

WARNINGS

WARNING: KEEP OUT OF EYES. DISCONTINUE USE IF IRRITATION OCCURS. KEEP OUT OF REACH OF CHILDREN

PACKAGE LABEL

PRINCIPAL DISPLAY PANEL:

MAC

SATINFINISH SPF 15

FOUNDATION

30 ML/1 FL OZ

DISTR BY MAKE-UP ART COSMETICS
TORONTO, ONTARIO, CANADA, M5V 1R7